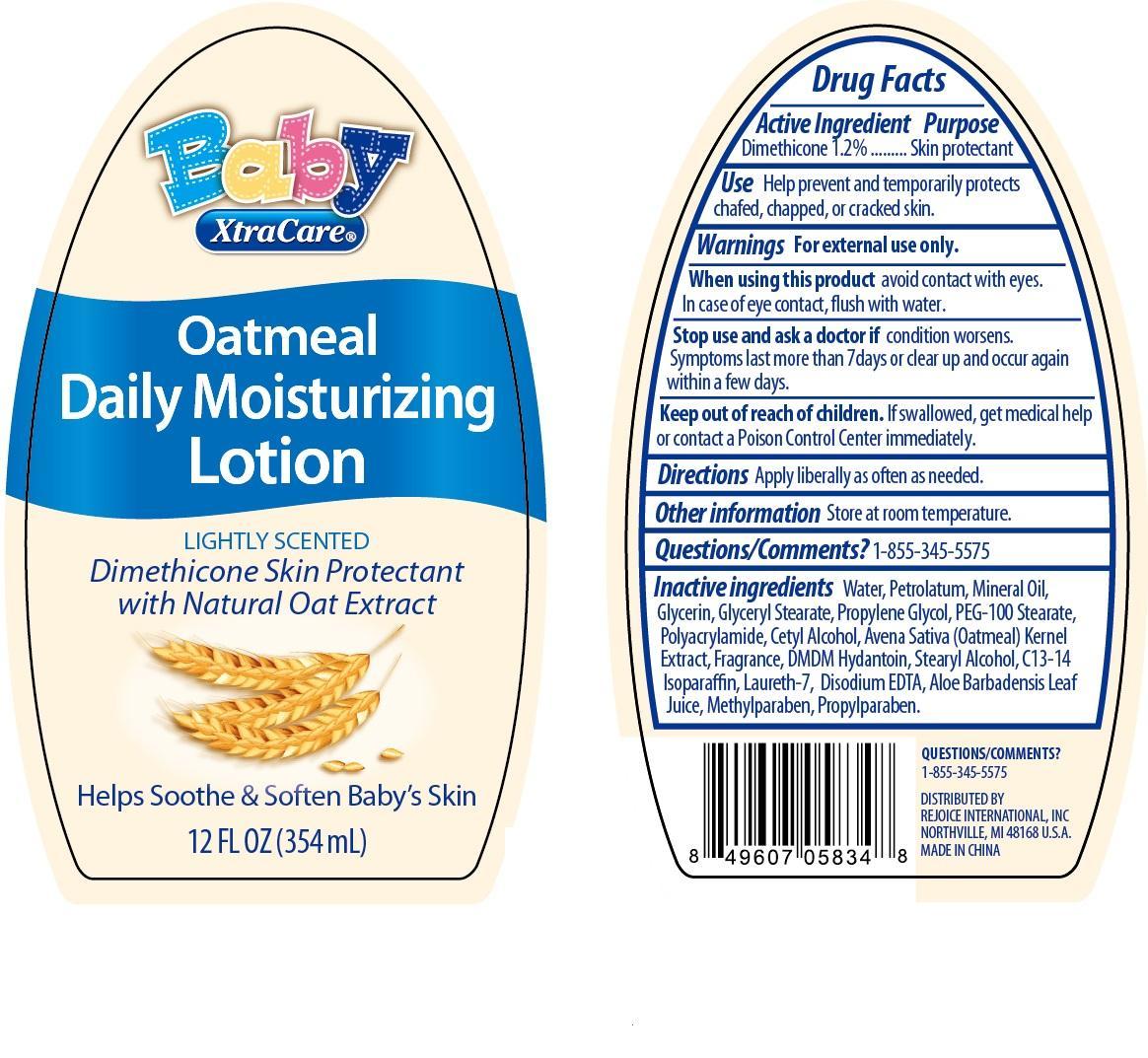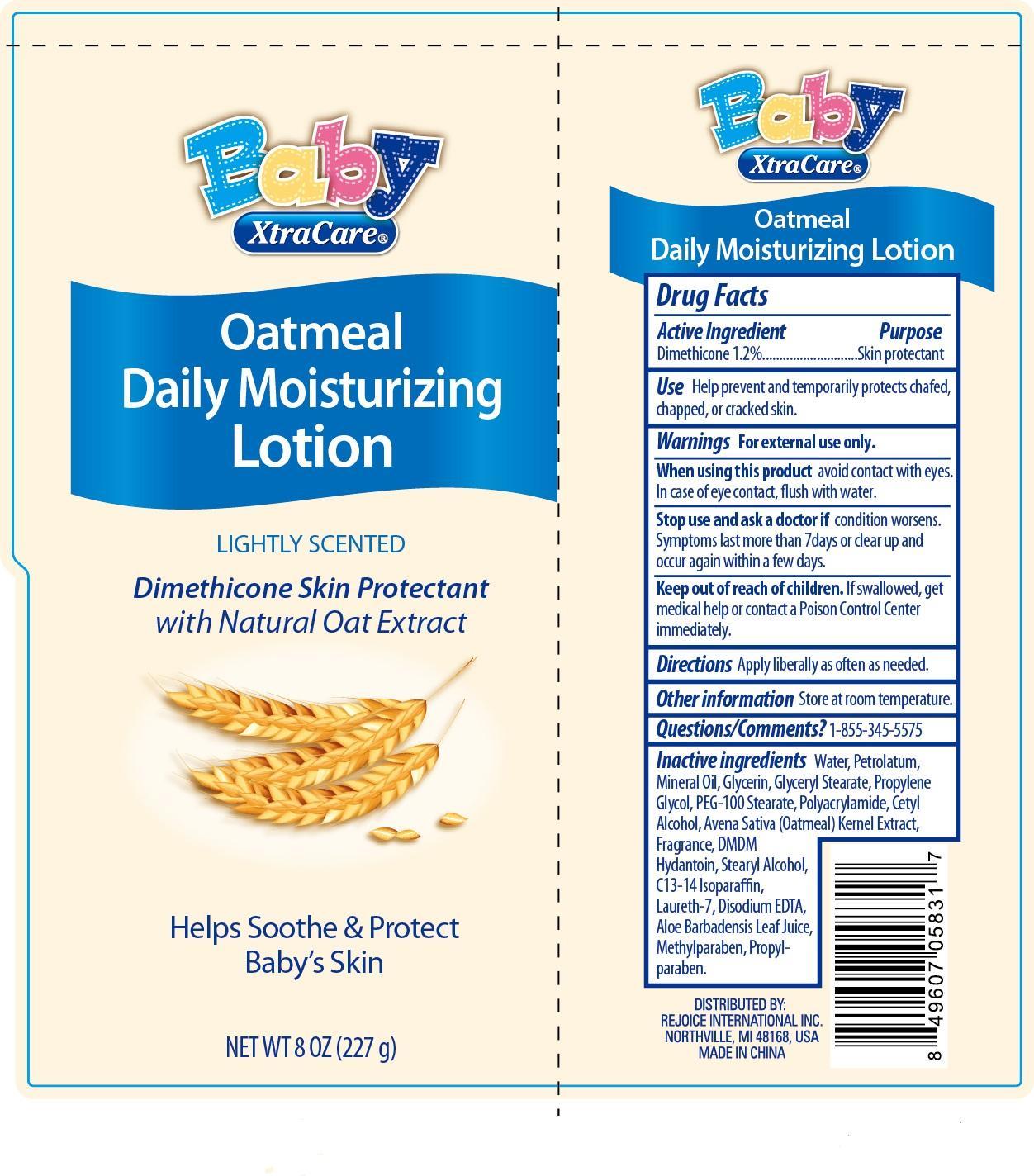 DRUG LABEL: Baby XtraCare Oatmeal
NDC: 57337-070 | Form: LOTION
Manufacturer: Rejoice International
Category: otc | Type: HUMAN OTC DRUG LABEL
Date: 20250123

ACTIVE INGREDIENTS: DIMETHICONE 1.2 g/100 g
INACTIVE INGREDIENTS: WATER; PETROLATUM; MINERAL OIL; GLYCERIN; GLYCERYL MONOSTEARATE; PROPYLENE GLYCOL; PEG-100 STEARATE; POLYACRYLAMIDE (10000 MW); CETYL ALCOHOL; AVENA SATIVA WHOLE; DMDM HYDANTOIN; STEARYL ALCOHOL; C13-14 ISOPARAFFIN; LAURETH-7; EDETATE DISODIUM; ALOE VERA LEAF; METHYLPARABEN; PROPYLPARABEN

Active Ingredient Purpose

Dimethicone 1.2% ............................ Skin Protectant

Use

Help prevent and temporarily protects chafed, chapped, or cracked skin.

Keep out of reach of children. If swallowed, get medical help or contact a Poison Control Center immediately.

INDICATIONS AND USAGE

Baby XtraCare®

Oatmeal Daily Moisturizing Lotion

Lightly Scented

Dimethicon Skin Protectant with Natural Oat Extract

Helps Soothe & Soften Baby's Skin

12 FL OZ (354 mL)

Directions

Apply liberally as often as needed.

Warnings

For extenal use only.

When using this product avoid contact with eyes. In case of eye contact, flush with water.

Stop use and ask a doctor if condition worsens. Symptoms last more than 7days or clear up and occur again within a few days.

Inactive Ingredients

water, petrolatum, mineral oil, glycerin, glyceryl stearate, propylene glycol, PEG-100 stearate, polyacrylamide, cetyl alcohol, avena sativa (oatmeal) kernel extract, fragrance, DMDM hydantoin, stearyl alcohol, c13-14 isoparaffin, laureth-7, disodium EDTA, aloe barbadensis leaf juice, methylparaben, propylparaben.

Other Information Store at room temperature.

Questions/Comments? 1-855-345-5575

DISTRIBUTED BY

REJOICE INTERNATIONAL INC

NORTHVILLE, MI 48168 U.S.A.

MADE IN CHINA